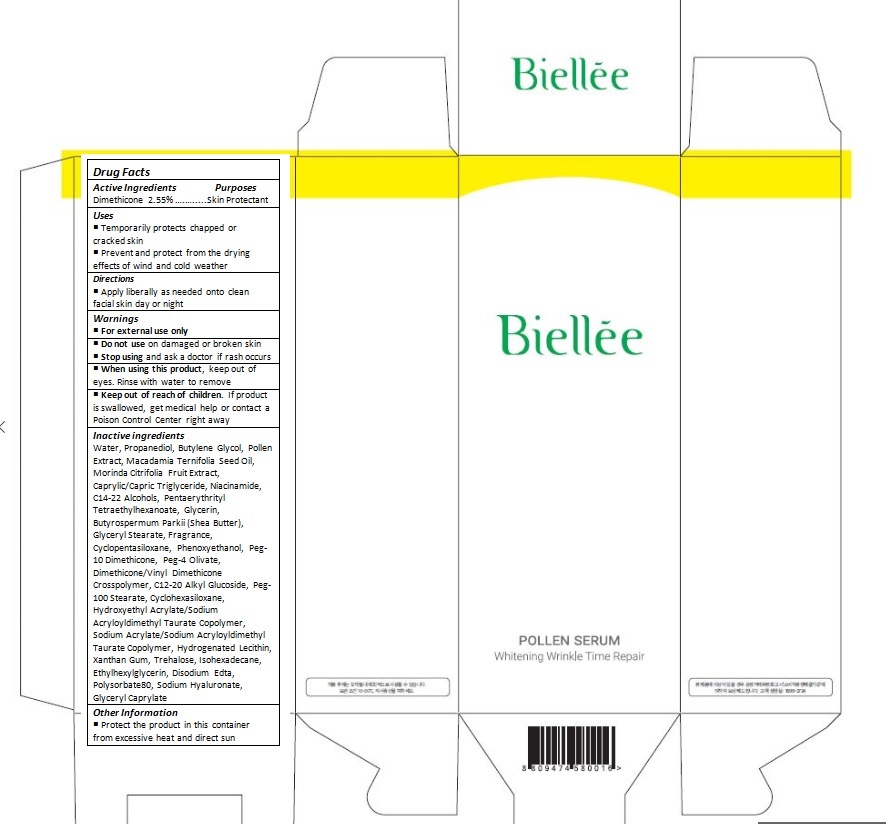 DRUG LABEL: Biellee Pollen Whitening Wrinkle Time Repair Serum
NDC: 70784-003 | Form: CREAM
Manufacturer: NSB CO., LTD.
Category: otc | Type: HUMAN OTC DRUG LABEL
Date: 20160622

ACTIVE INGREDIENTS: DIMETHICONE 1.02 mg/40 mL
INACTIVE INGREDIENTS: WATER; DIPROPYLENE GLYCOL; BEE POLLEN; MACADAMIA OIL; NONI FRUIT; MEDIUM-CHAIN TRIGLYCERIDES; NIACINAMIDE; C14-22 ALCOHOLS; PENTAERYTHRITYL TETRAETHYLHEXANOATE; GLYCERIN; SHEA BUTTER; GLYCERYL MONOSTEARATE; CYCLOMETHICONE 5; PHENOXYETHANOL; PEG-10 DIMETHICONE (600 CST); PEG-4 OLEATE; DIMETHICONE/VINYL DIMETHICONE CROSSPOLYMER (HARD PARTICLE); C12-20 ALKYL GLUCOSIDE; PEG-100 STEARATE; CYCLOMETHICONE 6; HYDROXYETHYL ACRYLATE/SODIUM ACRYLOYLDIMETHYL TAURATE COPOLYMER (100000 MPA.S AT 1.5%); SODIUM ACRYLATE/SODIUM ACRYLOYLDIMETHYLTAURATE COPOLYMER (4000000 MW); HYDROGENATED SOYBEAN LECITHIN; XANTHAN GUM; TREHALOSE; ISOHEXADECANE; ETHYLHEXYLGLYCERIN; EDETATE DISODIUM; POLYSORBATE 80; HYALURONATE SODIUM; GLYCERYL CAPRYLATE

Drug Facts

ACTIVE INGREDIENT

DIMETHICONE 2.55%

PURPOSE

Skin Protectant

INDICATIONS AND USAGE

Temporarily protects chapped or cracked skin
Prevent and protect from the drying effects of wind and cold weather

DOSAGE AND ADMINISTRATION

Apply liberally as needed onto clean facial skin day or night

WARNINGS

For external use only

Do not use on damaged or broken skin

When using this product, keep out of eyes. Rinse with water to remove.

Stop using and ask a doctor if rash occurs.

KEEP OUT OF REACH OF CHILDREN

Keep out of reach of the children. If product is swallowed, get medical help or contact a poison control center right away.

INACTIVE INGREDIENT

WATER
PROPANEDIOL
BUTYLENE GLYCOL
POLLEN EXTRACT
MACADAMIA TERNIFOLIA SEED OIL
MORINDA CITRIFOLIA FRUIT EXTRACT
CAPRYLIC/CAPRIC TRIGLYCERIDE
NIACINAMIDE
C14-22 ALCOHOLS
PENTAERYTHRITYL TETRAETHYLHEXANOATE
GLYCERIN
BUTYROSPERMUM PARKII (SHEA BUTTER)
GLYCERYL STEARATE
FRAGRANCE
CYCLOPENTASILOXANE
PHENOXYETHANOL
PEG-10 DIMETHICONE
PEG-4 OLIVATE
DIMETHICONE/VINYL DIMETHICONE CROSSPOLYMER
C12-20 ALKYL GLUCOSIDE
PEG-100 STEARATE
CYCLOHEXASILOXANE
HYDROXYETHYL ACRYLATE/SODIUM ACRYLOYLDIMETHYL TAURATE COPOLYMER
SODIUM ACRYLATE/SODIUM ACRYLOYLDIMETHYL TAURATE COPOLYMER
HYDROGENATED LECITHIN
XANTHAN GUM
TREHALOSE
ISOHEXADECANE
ETHYLHEXYLGLYCERIN
DISODIUM EDTA
POLYSORBATE80
SODIUM HYALURONATE
GLYCERYL CAPRYLATE